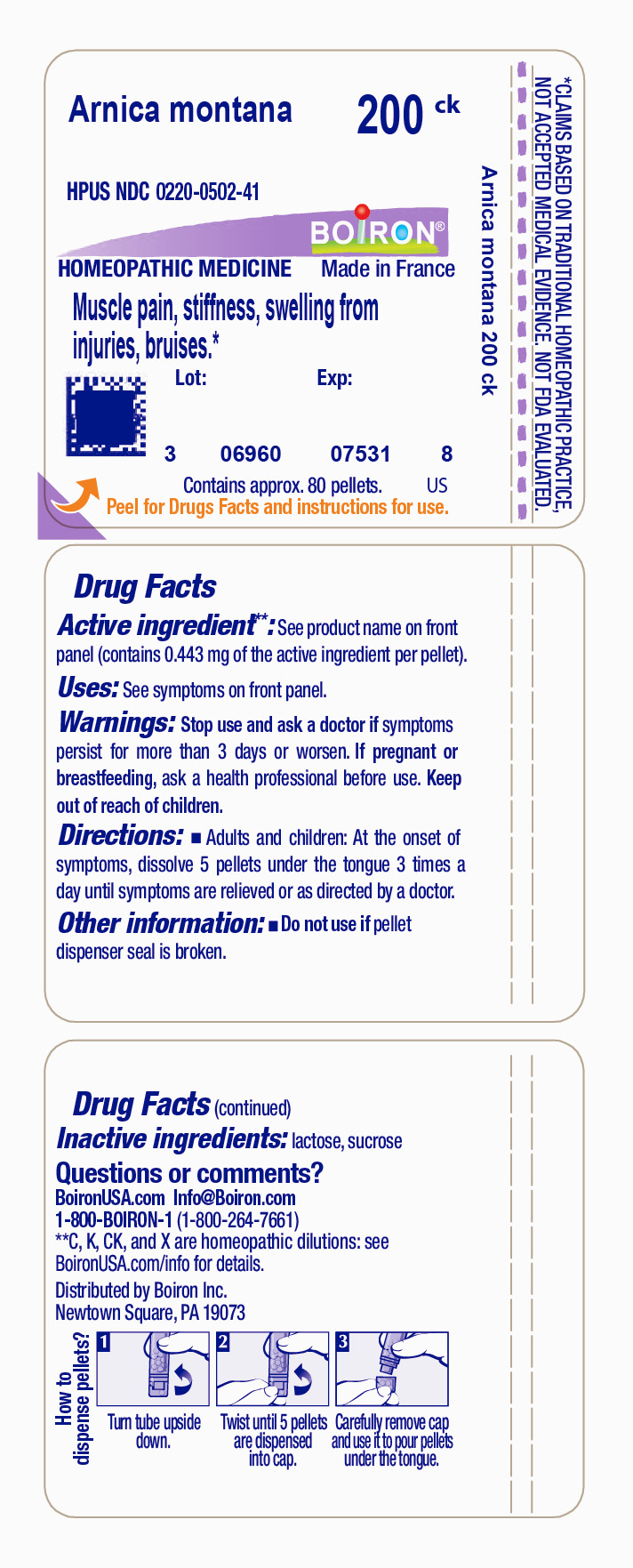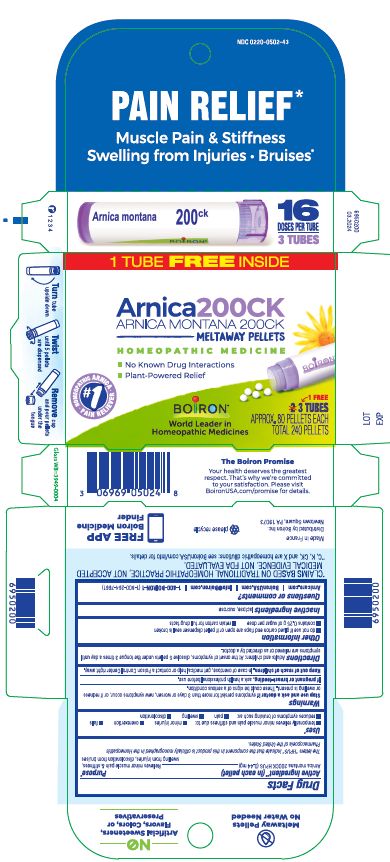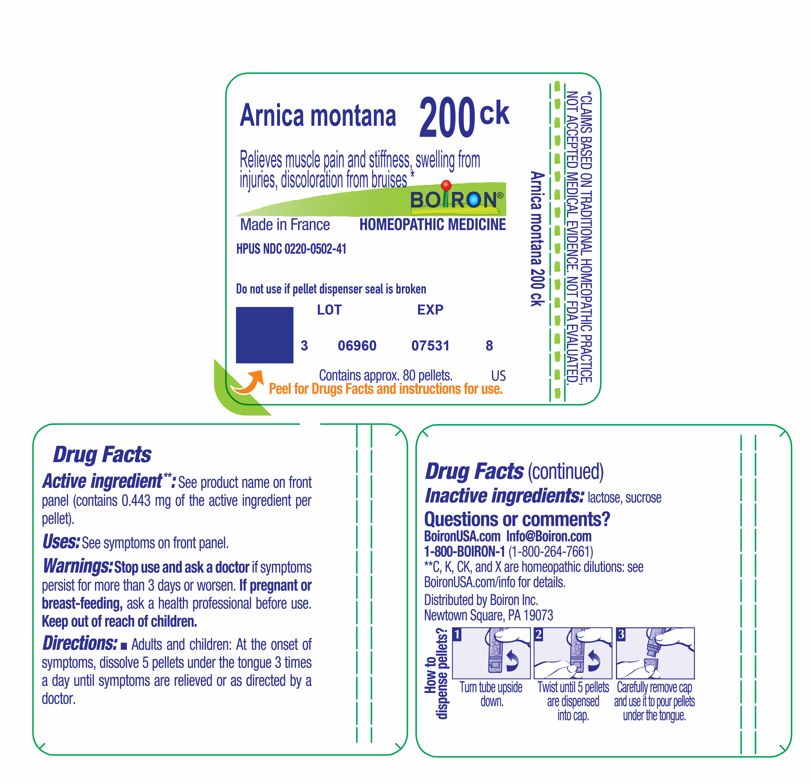 DRUG LABEL: Arnica montana
NDC: 0220-0502 | Form: PELLET
Manufacturer: Boiron
Category: homeopathic | Type: HUMAN OTC DRUG LABEL
Date: 20240521

ACTIVE INGREDIENTS: ARNICA MONTANA 200 [kp_C]/200 [kp_C]
INACTIVE INGREDIENTS: LACTOSE, UNSPECIFIED FORM; SUCROSE

Arnica montana 200CK

Active ingredient** (in each pellet)

Arnica montana 200CK HPUS (0.44 mg)

The letters "HPUS" indicate that the components in this product are officially monographed in the Homeopathic Pharmacopoeia of the United States.

Purpose*

Arnica montana 200CK HPUS (0.44 mg) ... Relieves muscle pain & stiffness, swelling from injuries, discoloration from bruises

Uses*

temporarily relieves minor muscle pain and stiffness due to:

- minor injuries
- overexertion
- falls

reduces symptoms of bruising such as:

- pain
- swelling
- discoloration

STOP USE

Box: Stop use and ask a doctor if symptoms persist for more than 3 days or worsen, new symptoms occur, or if redness or swelling is present. These could be a sign of a serious condition.

Tube: Stop use and ask a doctor if symptoms persist for more than 3 days or worsen.

PREGNANCY OR BREAST FEEDING

Box: If pregnant or breast-feeding, ask a health professional before use.

Tube: If pregnant or breast-feeding, ask a health professional before use.

KEEP OUT OF REACH OF CHILDREN

Box: Keep out of reach of children. In case of accidental overdose, get medical help or contact a Poison Control Center right away.

Tube: Keep out of reach of children.

Box:

Do not use if glued carton end flaps are open or if pellet dispenser seal is broken.

3 Tubes

Approx 80 pellets each

Total 240 pellets
16 Doses per tube

No known drug interactions

Plant-Powered Relief

Pain Relief*

Muscle Pain & Stiffness Swelling from Injuries Bruises*

Meltaway Pellets
How to dispense pellets? Turn tube upside down. Twist until 5 pellets are dispensed. Remove cap and pour pellets under the tongue

Tube:

Do not use if pellet dispenser seal is broken.
Contains approx 80 pellets.
How to dispense pellets? Turn tube upside down. Twist until 5 pellets are dispensed into cap. Carefully remove the cap and use it to pour pellets under the tongue.

*CLAIMS BASED ON TRADITIONAL HOMEOPATHIC PRACTICE NOT ACCEPTED MEDICAL EVIDENCE. NOT FDA EVALUATED.
*C,K,CK, and X are homeopathic dilutions: see BoironUSA.com/info for details.

INACTIVE INGREDIENT

lactose, sucrose

DOSAGE AND ADMINISTRATION

Adults and children: At the onset of symptoms, dissolve 5 pellets under the tongue 3 times a day until symptoms are relieved or as directed by a doctor.

QUESTIONS

Arnicare.com

BoironUSA.com

Info@Boiron.com

1-800-BOIRON-1 (1-800-264-7661)